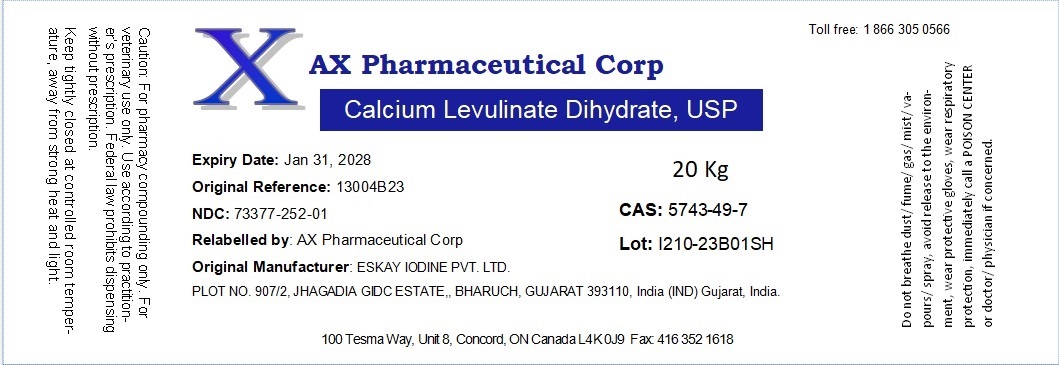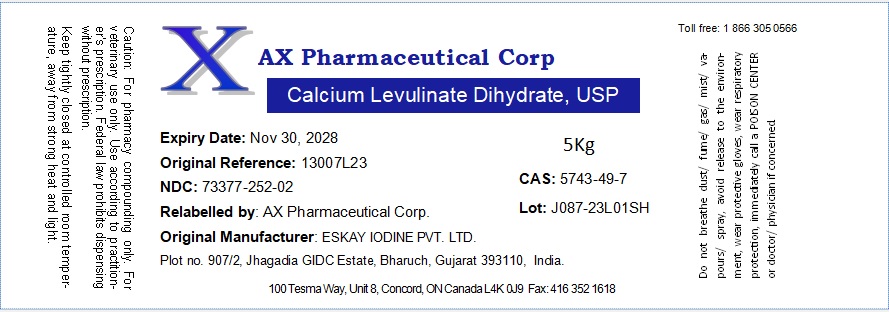 DRUG LABEL: Calcium Levulinate Dihydrate
NDC: 73377-252 | Form: POWDER
Manufacturer: AX Pharmaceutical Corp
Category: other | Type: BULK INGREDIENT - ANIMAL DRUG
Date: 20240716

ACTIVE INGREDIENTS: CALCIUM LEVULINATE 1 g/1 g

Calcium Levulinate Dihydrate